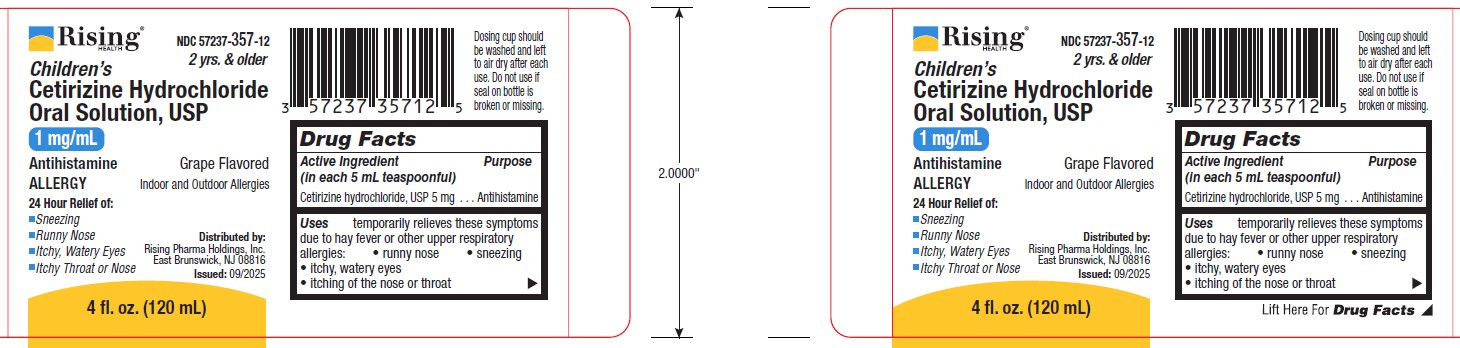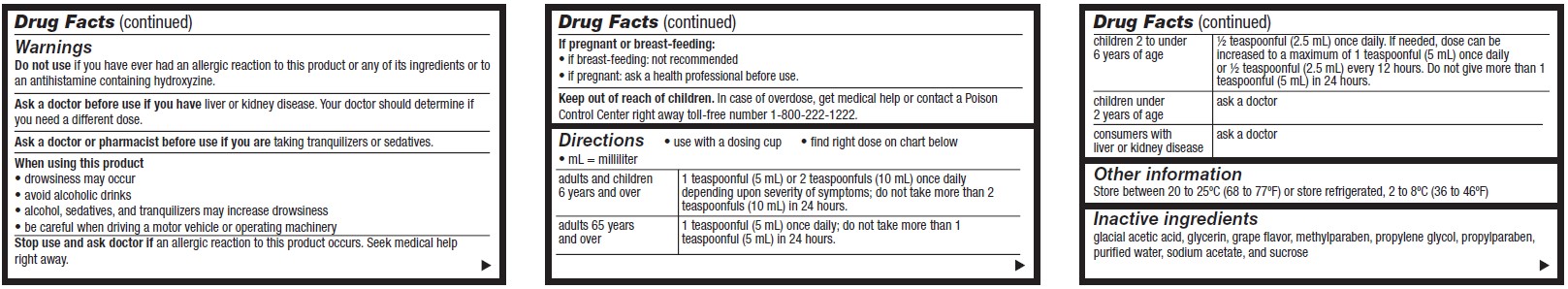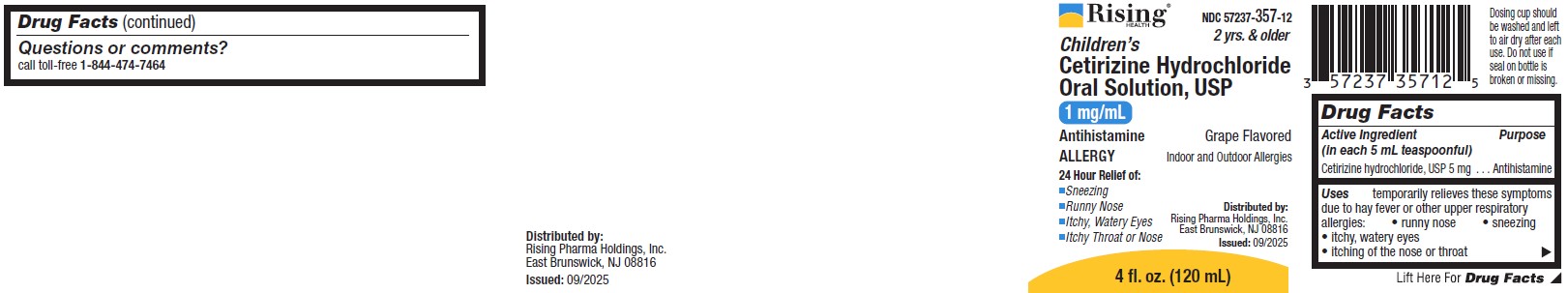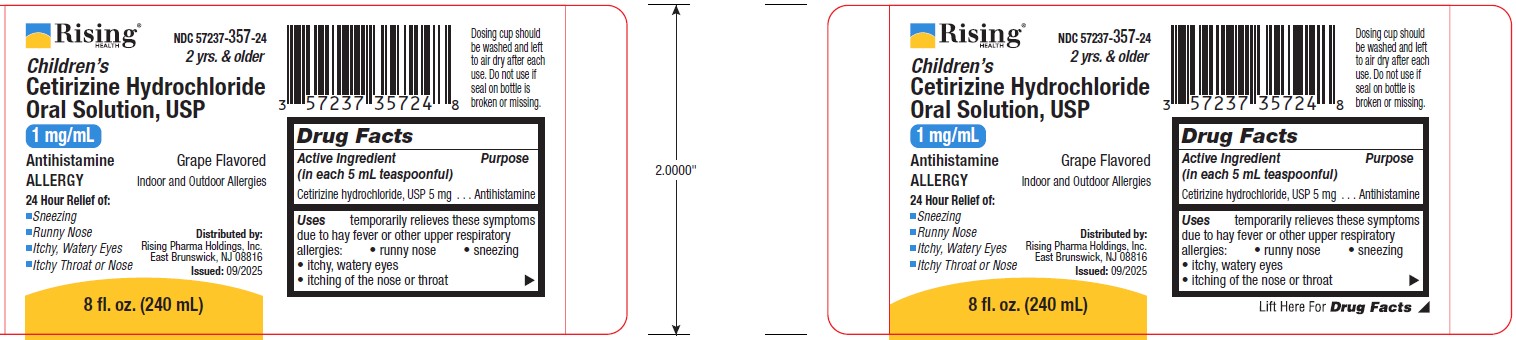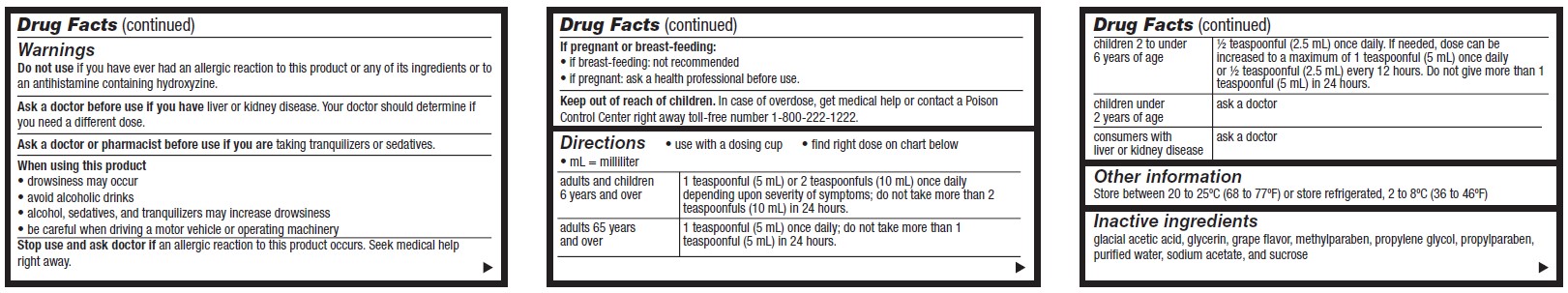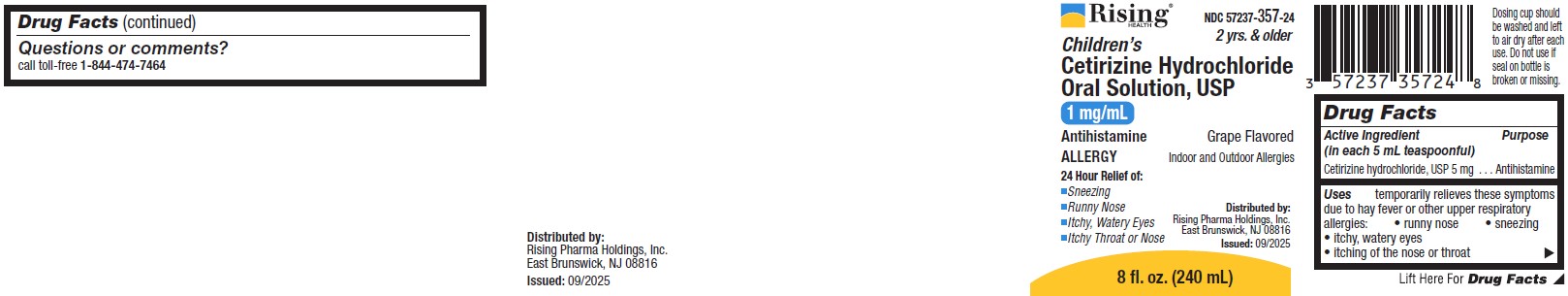 DRUG LABEL: CETIRIZINE HYDROCHLORIDE
NDC: 57237-357 | Form: SOLUTION
Manufacturer: Rising Pharma Holdings, Inc.
Category: otc | Type: HUMAN OTC DRUG LABEL
Date: 20251007

ACTIVE INGREDIENTS: CETIRIZINE HYDROCHLORIDE 1 mg/1 mL
INACTIVE INGREDIENTS: SUCROSE; SODIUM ACETATE; WATER; GLYCERIN; ACETIC ACID; METHYLPARABEN; PROPYLENE GLYCOL; PROPYLPARABEN

ALLERGY
Children’s Cetirizine Hydrochloride Oral Solution, USP
1 mg/mL
2 yrs. & older

Drug Facts

Active Ingredient (in each 5 mL teaspoonful)

Cetirizine hydrochloride, USP 5 mg

Purpose

Antihistamine

Uses

temporarily relieves these symptoms due to hay fever or other upper respiratory allergies:

- runny nose
- sneezing
- itchy, watery eyes
- itching of the nose or throat

Warnings

Do not use if you have ever had an allergic reaction to this product or any of its ingredients or to an antihistamine containing hydroxyzine.

Ask a doctor before use if you have liver or kidney disease. Your doctor should determine if you need a different dose.

Ask a doctor or pharmacist before use if you are taking tranquilizers or sedatives.

When using this product

- drowsiness may occur
- avoid alcoholic drinks
- alcohol, sedatives, and tranquilizers may increase drowsiness
- be careful when driving a motor vehicle or operating machinery

Stop use and ask a doctor if an allergic reaction to this product occurs. Seek medical help right away.

If pregnant or breast-feeding:

- if breast-feeding: not recommended
- if pregnant: ask a health professional before use.

Keep out of reach of children.

In case of overdose, get medical help or contact a Poison Control Center right away toll-free number 1-800-222-1222.

Directions

- use with a dosing cup
- find right dose on chart below
- mL = milliliter

adults and children 6 years and over | 1 teaspoonful (5 mL) or 2 teaspoonfuls (10 mL) once daily depending upon severity of symptoms; do not take more than 2 teaspoonfuls (10 mL) in 24 hours.
adults 65 years and over | 1 teaspoonful (5 mL) once daily; do not take more than 1 teaspoonful (5 mL) in 24 hours.
children 2 to under 6 years of age | ½ teaspoonful (2.5 mL) once daily. If needed, dose can be increased to a maximum of 1 teaspoonful (5 mL) once daily or ½ teaspoonful (2.5 mL) every 12 hours. Do not give more than 1 teaspoonful (5 mL) in 24 hours.
children under 2 years of age | ask a doctor
consumers with liver or kidney disease | ask a doctor

Other information

Store between 20 to 25ºC (68 to 77ºF) or store refrigerated, 2 to 8ºC (36 to 46ºF)

Inactive ingredients

glacial acetic acid, glycerin, grape flavor, methylparaben, propylene glycol, propylparaben, purified water, sodium acetate, and sucrose

Questions or comments?

call toll-free 1-844-474-7464

PRINCIPAL DISPLAY PANEL: 4 fl. oz. (120 mL) - NDC 57237-357-12

NDC 57237-357-12

Children’s 2 yrs. & older
Cetirizine Hydrochloride Oral Solution, USP
1 mg/mL

Antihistamine
Grape Flavored

ALLERGY

Indoor and Outdoor Allergies

24 Hour Relief of:
• Sneezing
• Runny Nose
• Itchy, Watery Eyes
• Itchy Throat or Nose

4 fl. oz. (120 mL)

Dosing cup should be washed and left to air dry after each use. Do not use if seal on bottle is broken or missing.

Distributed by:
Rising Pharma Holdings, Inc.
East Brunswick, NJ 08816
Issued: 09/2025

PRINCIPAL DISPLAY PANEL: 8 fl. oz. (240 mL) - NDC 57237-357-24

NDC 57237-357-24

Children’s 2 yrs. & older
Cetirizine Hydrochloride Oral Solution, USP

1 mg/mL

Antihistamine
Grape Flavored

ALLERGY

Indoor and Outdoor Allergies

24 Hour Relief of:
• Sneezing
• Runny Nose
• Itchy, Watery Eyes
• Itchy Throat or Nose

8 fl. oz. (240 mL)

Dosing cup should be washed and left to air dry after each use. Do not use if seal on bottle is broken or missing.

Distributed by:
Rising Pharma Holdings, Inc.
East Brunswick, NJ 08816
Issued: 09/2025